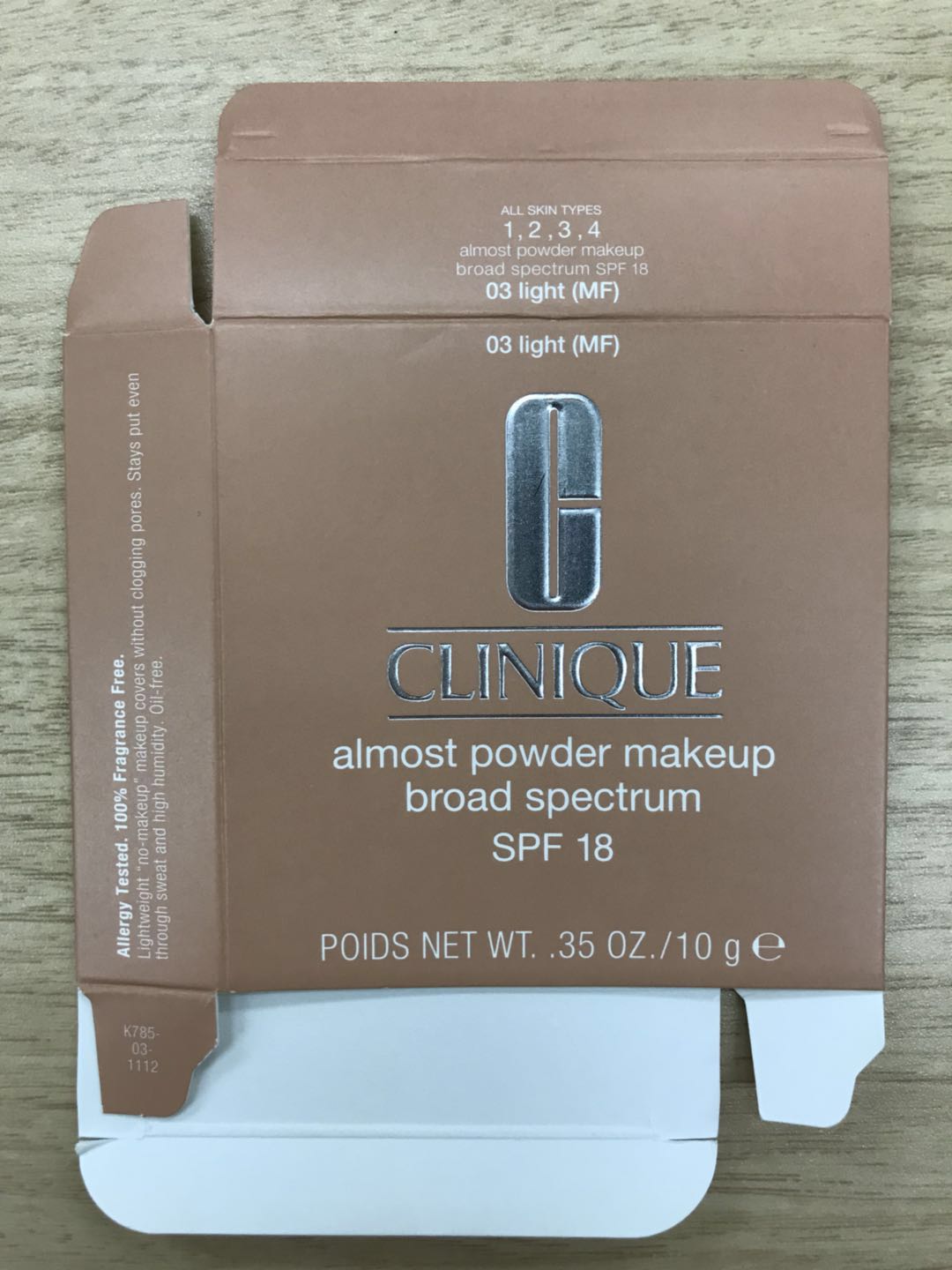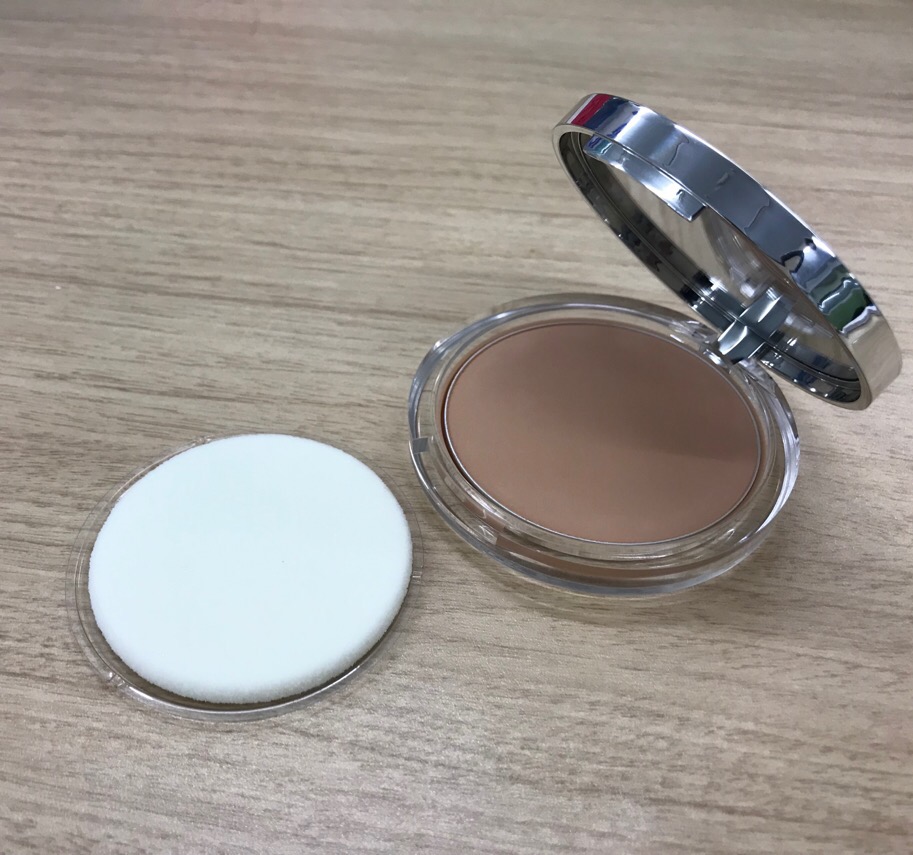 DRUG LABEL: ALMOST MAKEUP
NDC: 38001-801 | Form: POWDER
Manufacturer: ASANUMA CORPORATION
Category: otc | Type: HUMAN OTC DRUG LABEL
Date: 20201217

ACTIVE INGREDIENTS: TITANIUM DIOXIDE 1.23 g/100 g; ETHYLHEXYL METHOXYCRYLENE 2 g/100 g
INACTIVE INGREDIENTS: TALC; PHYTOSTERYL/ISOSTEARYL/CETYL/STEARYL/BEHENYL DIMER DILINOLEATE; HYALURONATE SODIUM; 1,2-HEXANEDIOL; FERROSOFERRIC OXIDE; PALMITIC ACID; METHICONE (20 CST); MICA; ASCORBYL TETRAISOPALMITATE; SODIUM PALMITOYL SARCOSINATE; ALUMINUM HYDROXIDE; BORON NITRIDE; SQUALANE; TOCOPHEROL; CETYL ETHYLHEXANOATE; DIISOSTEARYL MALATE; MAGNESIUM PALMITOYL GLUTAMATE; NYLON-12; PALMITOYL PROLINE; ALUMINUM OXIDE; FERRIC OXIDE RED; SILICON DIOXIDE; FERRIC OXIDE YELLOW; VINYL DIMETHICONE/METHICONE SILSESQUIOXANE CROSSPOLYMER; STANNIC OXIDE; HYDRATED SILICA; DIMETHICONE; GLYCERIN; SODIUM DEHYDROACETATE

Clinique Almost Powder Makeup Broad Spectrum SPF 18

Actives ingredients

Octinoxate 2.0%

Titanium Dioxide 1.2%

Purpose

Sunscreen

Use

helps prevent sunburn

Warnings

For external use only.

Do not use on damaged or broken skin.

When using this product keep out of eyes. Rinse with water to remove.

Stop use

Stop use and ask a doctor if rash occurs.

Keep out of reach of children. If product is swallowed, get medical help or contact a Poison Control Center right away.

Directions

For sunscreen use:
apply liberally 15 minutes before sun exposure.
reapply at least every two hours.
use a water resistant sunscreen if swimming or sweating

Sun Protection Measure.
Spending time in the sun increases your risk of skin cancer and early skin aging.

To decrease this risk, regularly use a sunscreen with a Broad Spectrum SPF value of 15 or higher and other sun protection measures including:
limited time in the sun, especially from 10 a.m. - 2 p.m.
wear long-sleeved shirts, pants, hats and sunglasses.
children under 6 months of age: ask a doctor

Inactive ingredients

TALC, DIMETHICONE, NYLON-12, SILICA, SQUALANE, BORON NITRIDE, VINYL DIMETHICONE/METHICONE SILSESQUIOXANE CROSSPOLYMER, CETYL ETHYLHEXANOATE, DIISOSTEARYL MALATE, PHYTOSTERYL/ISOSTEARYL/CETYL/STEARYL/BEHENYL DIMER DILINOLEATE, METHICONE, GLYCERIN, SODIUM HYALURONATE, MAGNESIUM PALMITOYL GLUTAMATE, SODIUM PALMITOYL SARCOSINATE, PALMITOYL PROLINE, ALUMINA, TOCOPHEROL, PALMITIC ACID, 1,2-HEXANEDIOL, HYDRATED SILICA, ASCORBYL TETRAISOPALMITATE, ALUMINUM HYDROXIDE, TIN OXIDE, SODIUM DEHYDROACETATE, [+/- MICA, IRON OXIDIES (CI 77491), IRON OXIDIES (CI 77492), IRON OXIDIES (CI 77499), TITANIUM DIOXIDE (CI 77891)] [ILN45192]

Other information

protect the product in this container from excessive heat and direct sun

Principal display panel

CLINIQUE almost powder makeup broad spectrum SPF 18

POIDS NET WT. .35 OZ/ 10 g